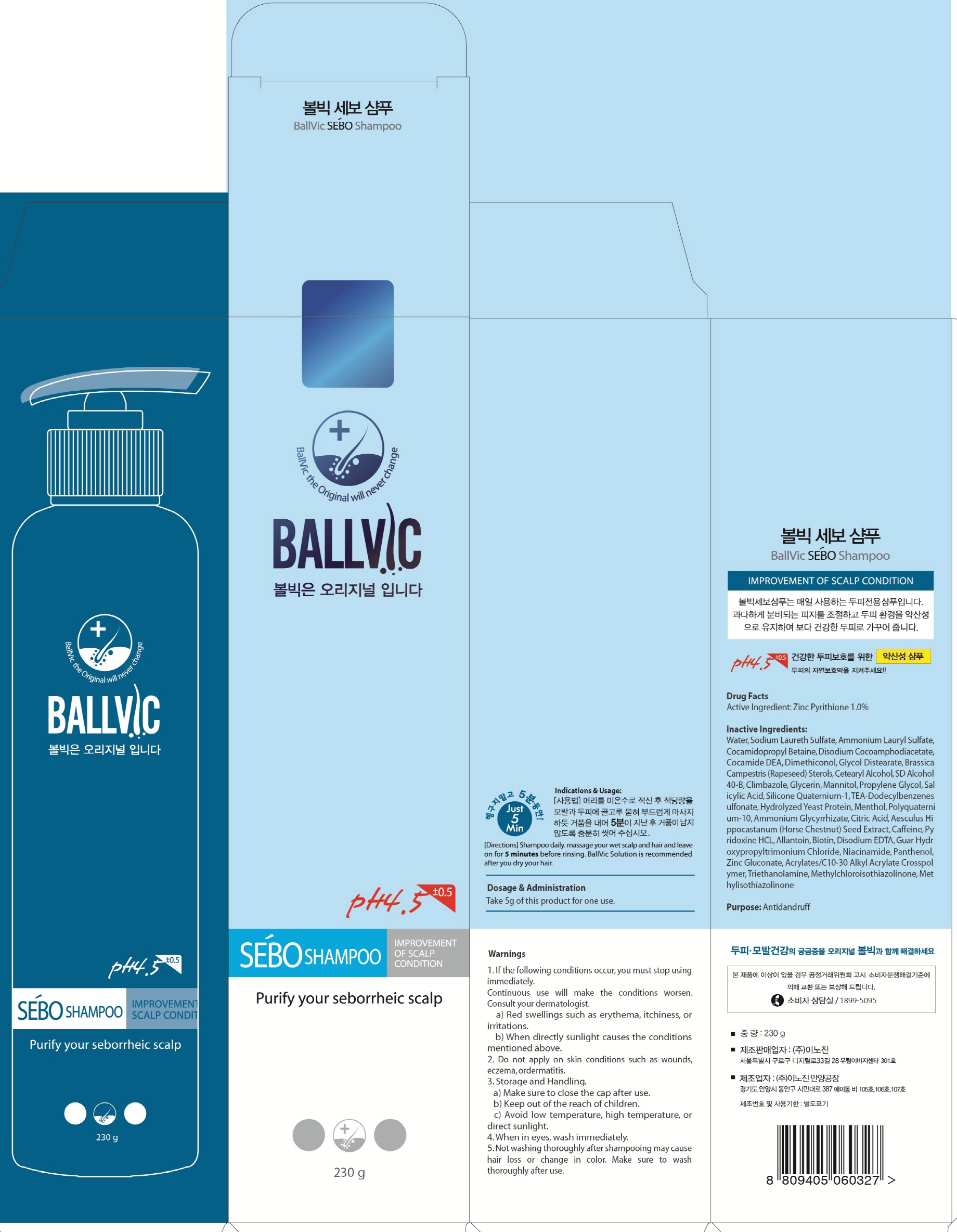 DRUG LABEL: BALLVIC SEBO
NDC: 70540-020 | Form: SHAMPOO
Manufacturer: INNOGENE CO.,LTD
Category: otc | Type: HUMAN OTC DRUG LABEL
Date: 20160321

ACTIVE INGREDIENTS: PYRITHIONE ZINC 2.3 g/230 g
INACTIVE INGREDIENTS: Water; Ammonium Lauryl Sulfate

ACTIVE INGREDIENT

Active Ingredient: Zinc Pyrithione 1.0%

INACTIVE INGREDIENT

Inactive Ingredients: Water, Sodium Laureth Sulfate, Ammonium Lauryl Sulfate, Cocamidopropyl Betaine, Disodium Cocoamphodiacetate, Cocamide DEA, Dimethiconol, Glycol Distearate, Brassica Campestris (Rapeseed) Sterols, Cetearyl Alcohol, SD Alcohol 40-B, Climbazole, Glycerin, Mannitol, Propylene Glycol, Salicylic Acid, Silicone Quaternium-1, TEA-Dodecylbenzenesulfonate, Hydrolyzed Yeast Protein, Menthol, Polyquaternium-10, Ammonium Glycyrrhizate, Citric Acid, Aesculus Hippocastanum (Horse Chestnut) Seed Extract, Caffeine, Pyridoxine HCL, Allantoin, Biotin, Disodium EDTA, Guar Hydroxypropyltrimonium Chloride, Niacinamide, Panthenol, Zinc Gluconate, Acrylates/C10-30 Alkyl Acrylate Crosspolymer, Triethanolamine, Methylchloroisothiazolinone, Methylisothiazolinone

PURPOSE

Purpose: Antidandruff

WARNINGS

Warnings: 1. If the following conditions occur, you must stop using immediately. Continuous use will make the conditions worsen. Consult your dermatologist. a. Red swellings such as erythema, itchiness, or irritations. b. When directly sunlight causes the conditions mentioned above. 2. Do not apply on skin conditions such as wounds, eczema, ordermatitis. 3. Storage and Handling. a. Make sure to close the cap after use. b. Keep out of the reach of children. c. Avoid low temperature, high temperature, or direct sunlight. 4. When in eyes, wash immediately. 5. Not washing thoroughly after shampooing may cause hair loss or change in color. Make sure to wash thoroughly after use.

KEEP OUT OF REACH OF CHILDREN

DIRECTIONS

Directions: Shampoo daily, massage your wel scalp and hair and leave on for 5 minutes before rinsing. BallVic Solution is recommended after you dry your hair.

DOSAGE & ADMINISTRATION

Dosage & Administration: Take 5g of this product for one use.